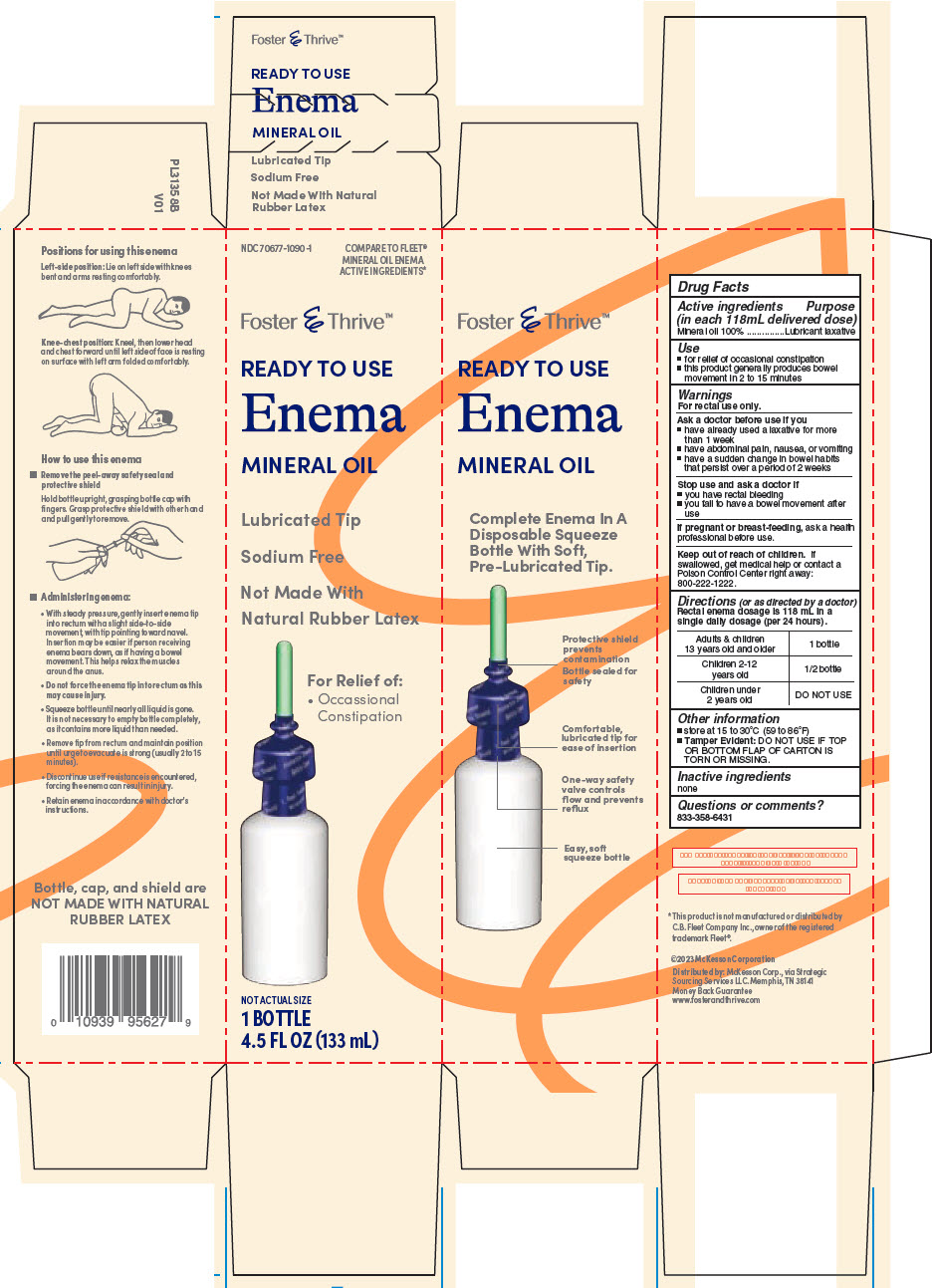 DRUG LABEL: Foster and Thrive Ready to Use Mineral oil 
NDC: 70677-1090 | Form: ENEMA
Manufacturer: McKesson
Category: otc | Type: HUMAN OTC DRUG LABEL
Date: 20240308

ACTIVE INGREDIENTS: Mineral Oil 1000 g/118 mL

Foster & Thrive™ Ready to Use Enema Mineral Oil
Laxative

Drug Facts

Active ingredients (in each 118mL delivered dose)

Mineral oil 100%

Purpose

Lubricant laxative

Use

- for relief of occasional constipation
- this product generally produces bowel movement in 2 to 15 minutes

Warnings

For rectal use only.

Ask a doctor before use if you

- have already used a laxative for more than 1 week
- have abdominal pain, nausea, or vomiting
- have a sudden change in bowel habits that persist over a period of 2 weeks

Stop use and ask a doctor if

- you have rectal bleeding
- you fail to have a bowel movement after use

PREGNANCY OR BREAST FEEDING

If pregnant or breast-feeding, ask a health professional before use.

Keep out of reach of children. If swallowed, get medical help or contact a Poison Control Center right away: 800-222-1222.

Directions (or as directed by a doctor)

Rectal enema dosage is 118 mL in a single daily dosage (per 24 hours).

Adults & children 13 years old and older | 1 bottle
Children 2-12 years old | 1/2 bottle
Children under 2 years old | DO NOT USE

Other information

- store at 15 to 30°C (59 to 86°F)
- Tamper Evident: DO NOT USE IF TOP OR BOTTOM FLAP OF CARTON IS TORN OR MISSING.

Inactive ingredients

none

Questions or comments?

833-358-6431

Distributed by: McKesson Corp., via Strategic
Sourcing Services LLC. Memphis, TN 38141

PRINCIPAL DISPLAY PANEL - 133 mL Bottle Carton

NDC 70677-1090-1

COMPARE TO FLEET®
MINERAL OIL ENEMA
ACTIVE INGREDIENTS*

Foster & Thrive™

READY TO USE
Enema
MINERAL OIL

Lubricated Tip

Sodium Free

Not Made With
Natural Rubber Latex

For Relief of:

- Occassional
  Constipation

NOT ACTUAL SIZE
1 BOTTLE
4.5 FL OZ (133 mL)